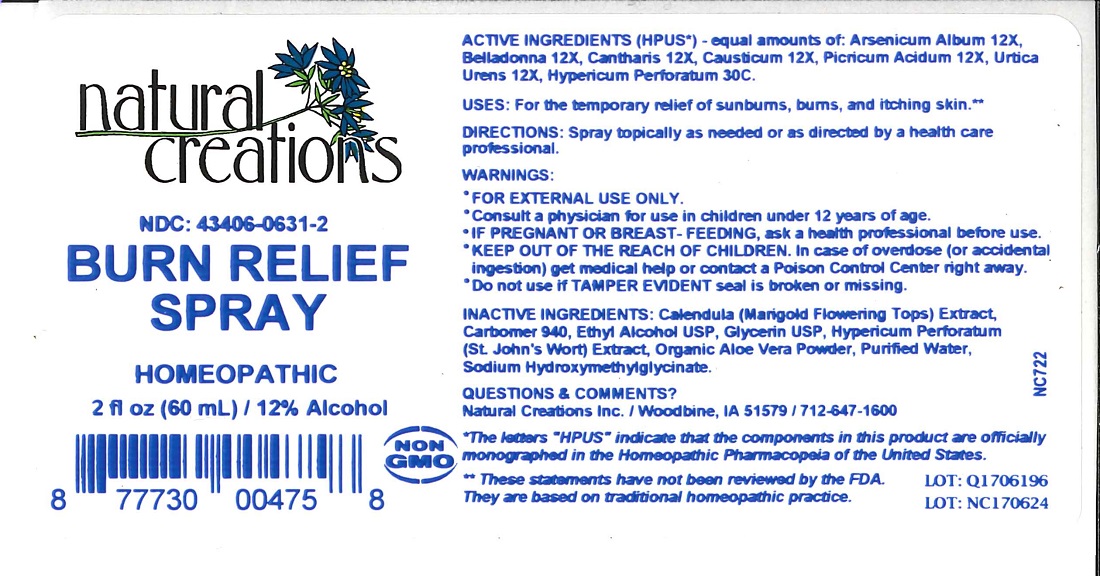 DRUG LABEL: BURN RELIEF
NDC: 43406-0631 | Form: SPRAY
Manufacturer: Natrural Creations, Inc.
Category: homeopathic | Type: HUMAN OTC DRUG LABEL
Date: 20251113

ACTIVE INGREDIENTS: ARSENIC TRIOXIDE 12 [hp_X]/1 mL; ATROPA BELLADONNA 12 [hp_X]/1 mL; LYTTA VESICATORIA 12 [hp_X]/1 mL; CAUSTICUM 12 [hp_X]/1 mL; PICRIC ACID 12 [hp_X]/1 mL; URTICA URENS 12 [hp_X]/1 mL; HYPERICUM PERFORATUM 30 [hp_C]/1 mL
INACTIVE INGREDIENTS: CALENDULA OFFICINALIS FLOWERING TOP; CARBOMER 940; ALCOHOL; GLYCERIN; HYPERICUM PERFORATUM FLOWER; ALOE VERA LEAF; WATER; SODIUM HYDROXYMETHYLGLYCINATE

BURN RELIEF SPRAY

ACTIVE INGREDIENT

Active Ingredients (HPUS*): Arsenicum Album 12X, Belladonna 12X, Cantharis 12X, Causticum 12X, Picricum Acidum 12X, Urtica Urens 12X, Hypericum Perforatum 30C.

PURPOSE

Uses: For the temporary relief of sunburns, burns, and itching skin.**

INDICATIONS AND USAGE

Uses: For the temporary relief of sunburns, burns, and itching skin.**

DOSAGE AND ADMINISTRATION

Directions: Spray topically as needed or as directed by a health care professional.

KEEP OUT OF REACH OF CHILDREN

KEEP OUT OF THE REACH OF CHILDREN. In case of overdose (or accidental ingestion) get medical help or contact a Poison Control Center right away.

WARNINGS:

- FOR EXTERNAL USE ONLY.
- Consult a physician for use in children under 12 years of age.
- IF PREGNANT OR BREAST-FEEDING, ask a health care professional before use.
- KEEP OUT OF THE REACH OF CHILDREN. In case of overdose (or accidental ingestion) get medical help or contact a Poison Control Center right away.
- Do no use if TAMPER EVIDENT seal is broken or missing.

INACTIVE INGREDIENT

Inactive Ingredients: Calendula (Marigold Flowering Tops) Extract, Carbomer 940, Ethyl Alcohol USP, Glycerin USP, Hypericum Perforatum (St. John's Wort) Extract, Organic Aloe Vera Powder, Purified Water, Sodium Hydroxymethylglycinate.

Questions & Comments?

Natural Creations, Inc. / Woodbine, IA 51579 / 712-647-1600

REFERENCES

*The letters "HPUS" indicate the components in this product are officially monographed in the Homoepathic Pharmacopeia of the United States.

**These statements have not been reviewed by the FDA. They are based on traditional homeopathic practice.

PACKAGE LABEL

NDC: 43406-0631-2

BURN RELIEF SPRAY

HOMEOPATHIC

2 fl oz (60 mL) / 12% Alcohol

UPC: 877730004758